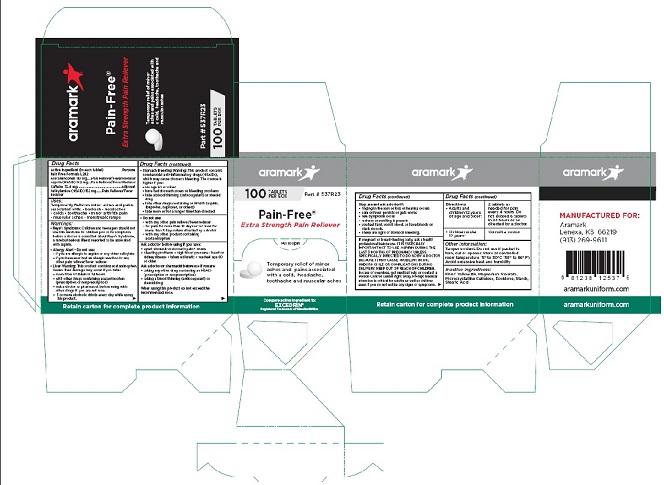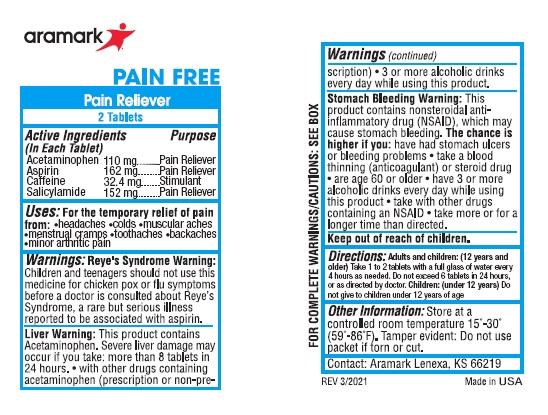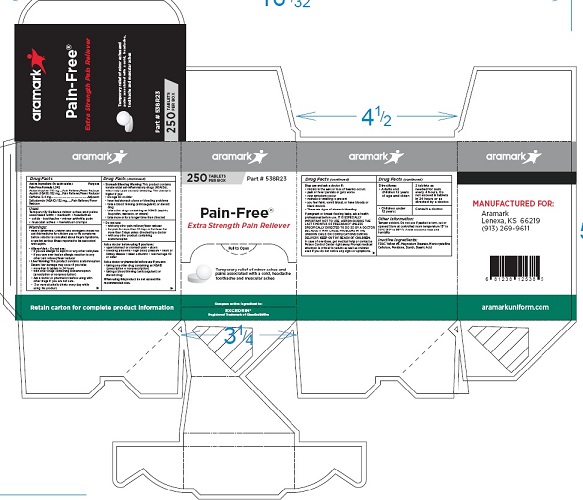 DRUG LABEL: Aramark Pain Free
NDC: 81238-0242 | Form: TABLET
Manufacturer: Western First Aid Safety DBA Aramark
Category: otc | Type: HUMAN OTC DRUG LABEL
Date: 20210603

ACTIVE INGREDIENTS: ACETAMINOPHEN 110 mg/1 1; ASPIRIN 162 mg/1 1; CAFFEINE 32.4 mg/1 1; SALICYLAMIDE 152 mg/1 1
INACTIVE INGREDIENTS: FD&C YELLOW NO. 6; MAGNESIUM STEARATE; MICROCRYSTALLINE CELLULOSE; POVIDONE; STARCH, CORN; STEARIC ACID

Aramark Pain-Free Extra Strength Pain Reliever

Drug Facts

Active Ingredient (in each tablet)
Pain Free Formula L242

Acetaminophen 110 mg
Aspirin (NSAID) 162 mg
Caffeine 32.4 mg
Salicylamide (NSAID) 152 mg

Purpose

Acetaminophen ...............Pain Reliever/Fever Reducer
Aspirin (NSAID) ...............Pain Reliever/Fever Reducer
Caffeine ...........................................................Adjuvent
Salicylamide (NSAID) .......Pain Reliever/Fever Reducer

Uses:
Temporarily Relieves minor aches and pains
associated with: • backach • headaches
• colds • toothache • minor arthritis pain
• muscular aches • menstrual cramps

Warnings:
• Reye’s Syndrome: Children and teenagers should not
use this medicine for chicken pox or flu symptoms
before a doctor is consulted about Reye’s Syndrome,
a rare but serious illness reported to be assocated
with aspirin.
• Allergy Alert - Do not use:
• if you are allergic to aspirin or any other salicylate
• if you have ever had an allergic reaction to any
other pain reliever/fever reducer
• Liver Warning: This product contains acetaminophen.
Severe liver damage may occur if you take:
• more than 8 tablets in 24 hours
• with other drugs containing acetaminophen
(prescription or nonprescription)
• Ask a doctor or pharmacist before using with
other drugs if you are not sure.
• 3 or more alcoholic drinks every day while using
this product.

• Stomach Bleeding Warning: This product contains
nonsteroidal anti-inflammatory drugs (NSAIDs),
which may cause stomach bleeding. The chance is
higher if you:
• are age 60 or older
• have had stomach ulcers or bleeding problems
• take a blood thinning (anticoagulant) or steroid
drug
• take other drugs containing an NSAID (aspirin,
ibuprofen, naproxen, or others)
• take more or for a longer time than directed
• Do not use:
• with any other pain reliever/fever reducer
• for pain for more than 10 days or for fever for
more than 3 days unless directed by a doctor
• with any other product containing
acetaminophen

Ask a doctor before using if you have:
• upset stomach or stomach pain • ulcers
• bleeding problems • high blood pressure • heart or
kidney disease • taken a diuretic • reached age 60
or older
Ask a doctor or pharmacist before use if you are:
• taking any other drug containing an NSAID
(prescription or nonprescription)
• taking a blood thinning (anticoagulant) or
steroid drug
When using this product do not exceed the
recommended dose.

Stop use and ask a doctor if:
• ringing in the ears or loss of hearing occurs
• pain or fever persists or gets worse
• new symptoms occur
• redness or swelling is present
• you feel faint, vomit blood, or have bloody or
black stoools.
• These are signs of stomach bleeding.

PREGNANCY OR BREAST FEEDING

If pregnant or breast-feeding baby, ask a health
professional before use. IT IS ESPECIALLY
IMPORTANT NOT TO USE ASPIRIN DURING THE
LAST 3 MONTHS OF PREGNANCY UNLESS
SPECIFICALLY DIRECTED TO DO SO BY A DOCTOR
BECAUSE IT MAY CAUSE PROBLEMS IN THE
UNBORN CHILD OR COMPLICATIONS DURING
DELIVERY.

KEEP OUT OF REACH OF CHILDREN.
In case of overdose, get medical help or contact a
Poison Control Center right away. Prompt medical
attention is critical for adults as well as children
even if you do not notice any signs or symptoms.

DOSAGE AND ADMINISTRATION

Directions: • Adults and children 12 years of age and older: | 2 tablets as; needed for pain every 4 hours. Do not exceed 8 tablets in 24 hours or as directed by a doctor.
• Children under 12 years: | Consult a doctor.

Other Information:
Tamper evident. Do not use if packet is
torn, cut or opened Store at controlled
room temperature 15° to 30°C (59° to 86° F)
Avoid excessive heat and humidity

Inactive Ingredients:
FD&C Yellow #6, Magnesium Stearate,
Microcrystalline Cellulose, Povidone, Starch,
Stearic Acid

Product Package

aramark

Pain-Free®

Extra Strength Pain Reliever

Temporary relief of minor
aches and pains associated with
a cold, headache, toothache and
muscular aches

Part # 537R23

100 TABLETS

PER BOX

Compare active ingredient to:

EXCEDRIN®
Registered Trademark of GlaxoSmithKline

Retain carton for complete product information

MANUFACTURED FOR:

Aramark
Lenexa, KS 66219
(913) 269-9611

aramarkuniform.com

100 Tablet Box

250 Tablet Box

2-Tablet packet

res